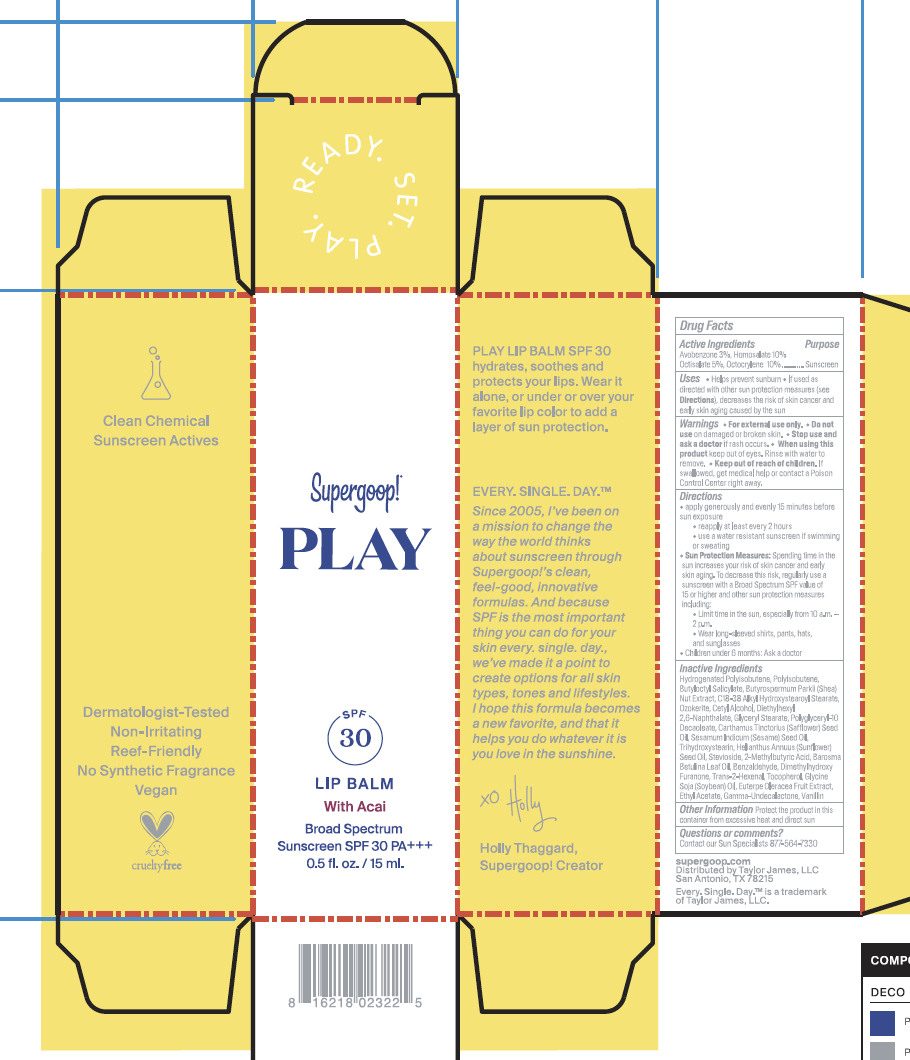 DRUG LABEL: Play Lip Balm with Acai Broad Spectrum SPF 30
NDC: 75936-225 | Form: STICK
Manufacturer: Supergoop, LLC
Category: otc | Type: HUMAN OTC DRUG LABEL
Date: 20241204

ACTIVE INGREDIENTS: HOMOSALATE 10 g/100 mL; AVOBENZONE 3 g/100 mL; OCTOCRYLENE 10 g/100 mL; OCTISALATE 5 g/100 mL
INACTIVE INGREDIENTS: ETHYL ACETATE; SHEANUT; BUTYLOCTYL SALICYLATE; GLYCERYL MONOSTEARATE; SAFFLOWER OIL; SESAME OIL; .GAMMA.-UNDECALACTONE; 2-METHYLBUTYRIC ACID; ACAI; AGATHOSMA BETULINA LEAF OIL; VANILLIN; HYDROGENATED POLYBUTENE (1300 MW); CERESIN; CETYL ALCOHOL; POLYGLYCERYL-10 DECAOLEATE; SUNFLOWER OIL; STEVIOSIDE; BENZALDEHYDE; DIMETHYLHYDROXY FURANONE; 2-HEXENAL, (2E)-; TOCOPHEROL; SOYBEAN OIL; TRIHYDROXYSTEARIN; POLYISOBUTYLENE (1300 MW); DIETHYLHEXYL 2,6-NAPHTHALATE

Play Lip Balm with Acai Broad Spectrum Sunscreen SPF 30

Active Ingredients Purpose

Avobenozone 3% Sunscreen

Homosalate 10% Sunscreen

Octisalate 5% Sunscreen

Octocrylene 10% Sunscreen

Uses
Helps Prevent Sunburn
If used as directed with other sun protection measures (see Directions), decreases the risk of skin cancer and early skin aging caused by the sun.

Keep out of reach of children.
If product is swallowed, get medical help or contact a poison Control Center right away

Stop use and ask a doctor if rash occurs.

Warnings

For external use only

Do not use on damaged or broken skin

When using this product keep out of eyes. Rinse with water to remove

Directions
Apply generously and evenly 15 minutes before sun exposure
Reapply at least every 2 hours.

Use a water-resistant sunscreen if swimming or sweating

Sun Protection Measures Spending time in the sun increases your risk of
skin cancer and early skin aging. To decrease this risk, regularly use a
sunscreen with a Broad-Spectrum SPF value of 15 or higher and other sun
protection measures including: • limit your time in the sun, especially from 10
a.m. – 2 p.m. • wear long-sleeved shirts, pants, hats, and sunglasses •
Children under 6 months of age: ask a doctor.

Inactive ingredients

Hydrogenated Polyisobutene, Polyisobutene, Butyloctyl Salicylate, Butyrospermum Parkii (Shea) Butter, C18-38 Alkyl Hydroxystearoyl Stearate, Ozokerite, Cetyl Alcohol, Diethylhexyl 2,6-Naphthalate, Glyceryl Stearate, Polyglyceryl-10 Decaoleate, Carthamus Tinctorius (Safflower) Seed Oil, Sesamum Indicum (Sesame) Seed Oil, Trihydroxystearin, Helianthus Annuus (Sunflower) Seed Oil, Stevioside, 2-Methylbutyric Acid, Barosma Betulina Leaf Oil, Benzaldehyde, Dimethylhydroxy Furanone, Trans-2-Hexenal, Tocopherol, Glycine Soja (Soybean) Oil, Euterpe Oleracea Fruit Extract, Ethyl Acetate, Gamma-Undecalactone, Vanilin

PACKAGE LABEL

Supergoop!

PLAY

SPF 30

LIP BALM with Acai

Broad Spectrum Sunscreen SPF 30

0.5 fl. oz./ 15 ml.